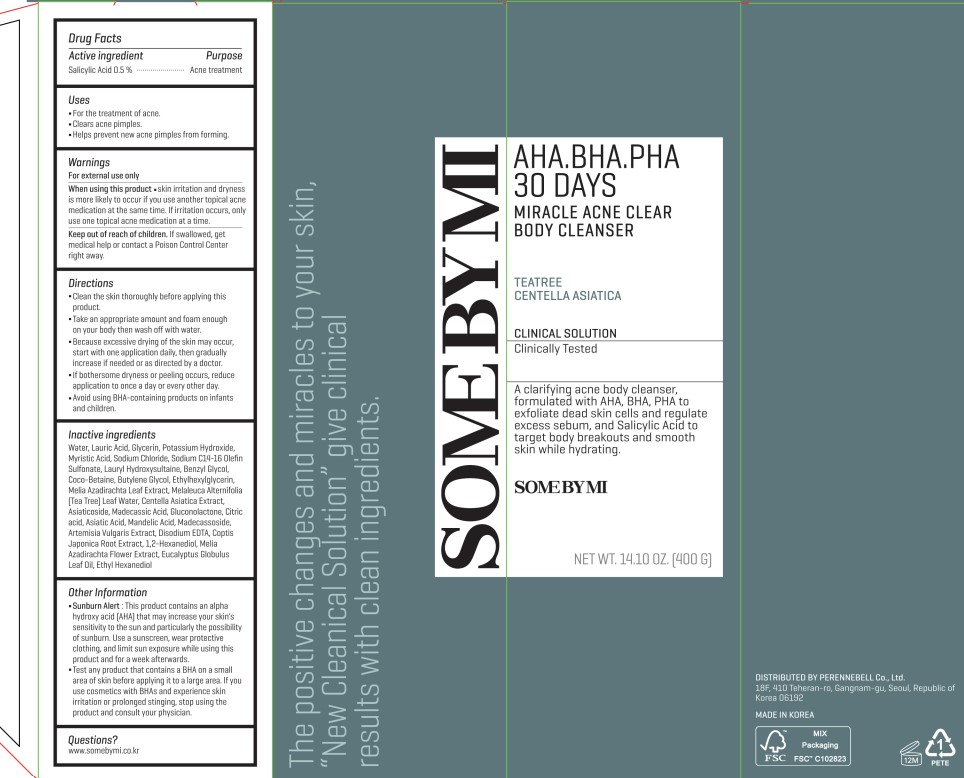 DRUG LABEL: SOME BY MI AHA BHA PHA 30 DAYS MIRACLE ACNE BODY CLEANSER
NDC: 74472-102 | Form: CREAM
Manufacturer: PERENNEBELL Co., Ltd.
Category: otc | Type: HUMAN OTC DRUG LABEL
Date: 20260105

ACTIVE INGREDIENTS: SALICYLIC ACID 2 g/400 g
INACTIVE INGREDIENTS: LAURIC ACID; GLYCERIN; SODIUM CHLORIDE; LAURYL HYDROXYSULTAINE; ETHYLHEXYLGLYCERIN; EDETATE DISODIUM ANHYDROUS; COPTIS JAPONICA ROOT; 1,2-HEXANEDIOL; AZADIRACHTA INDICA FLOWER; CENTELLA ASIATICA TRITERPENOIDS; MELALEUCA ALTERNIFOLIA (TEA TREE) LEAF OIL; ASIATICOSIDE; MADECASSIC ACID; ETHYLENE GLYCOL MONOBENZYL ETHER; WATER; AZADIRACHTA INDICA LEAF; ETHOHEXADIOL; MADECASSOSIDE; MANDELIC ACID; GLUCONOLACTONE; CITRIC ACID MONOHYDRATE; ASIATIC ACID; BUTYLENE GLYCOL; POTASSIUM HYDROXIDE; COCO-BETAINE; EUCALYPTUS OIL; MYRISTIC ACID; SODIUM C14-16 OLEFIN SULFONATE

SOME BY MI AHA BHA PHA 30 DAYS MIRACLE ACNE BODY CLEANSER

ACTIVE INGREDIENT

Salicylic acid 0.5%

INDICATIONS AND USAGE

■ For the treatment of acne.

■ Clears acne pimples.

■ Helps prevevnt new acne pimples from forming.

WARNINGS

For external use only
When using this product ■ skin irritation and dryness is more likely to occur if you use another topical acne medication at the same time. If irritation occurs, only use one topical acne medication at a time.
Keep out of reach of children. If swallowed, get medical help or contact a Poison Control Center right away.

KEEP OUT OF REACH OF CHILDREN

If swallowed, get medical help or contact a Poison Control Center right away.

WHEN USING

■ skin irritation and dryness is more likely to occur if tyou use another topcial acne medication at the same time. If irritation occurs, only use one topical acne medication at a time.

INACTIVE INGREDIENT

Water, Lauric Acid, Glycerin, Potassium Hydroxide, Myristic Acid, Sodium Chloride, Sodium C14-16 Olefin Sulfonate, Lauryl Hydroxysultaine, Benzyl Glycol, Coco-Betaine, Butylene Glycol, Ethylhexylglycerin, Melia Azadirachta Leaf Extract, Melaleuca Alternifolia [Tea Tree] Leaf Water, Centella Asiatica Extract, Asiaticoside, Madecassic Acid, Gluconolactone, Citric acid, Asiatic Acid, Mandelic Acid, Madecassoside, Artemisia Vulgaris Extract, Disodium EDTA, Coptis Japonica Root Extract, 1,2-Hexanediol, Melia Azadirachta Flower Extract, Eucalyptus Globulus Leaf Oil, Ethyl Hexanediol

OTHER SAFETY INFORMATION

■ Sunburn Alert: This product contains an alpha hydroxy acid [AHA] that may increase your skin's sensitivity to the sun and particularly the possibility of sunburn. Use a sunscreen, wear protective clothing, and limit sun exposure while using this product and for a week afterwards.

■Test any product that contains a BHA on a small area of skin before applying it to a large area. If you use cosmetics with BHAS and experience skin irritation or prolonged stinging, stop using the product and consult your physician.

SUNBURN ALERT

PURPOSE

Acne treatment

INSTRUCTIONS FOR USE

■Clean the skin thoroughly before applying this product.
■Take an appropriate amount and foam enough on your face then wash off with water.
■Because excessive drying of the skin may occur, start with one application daily, then gradually increase if needed or as directed by a doctor.

■If bothersome dryness or peeling occurs, reduce application to once a day or every other day.

■ Avoid using BHA-containing products on infants and children.